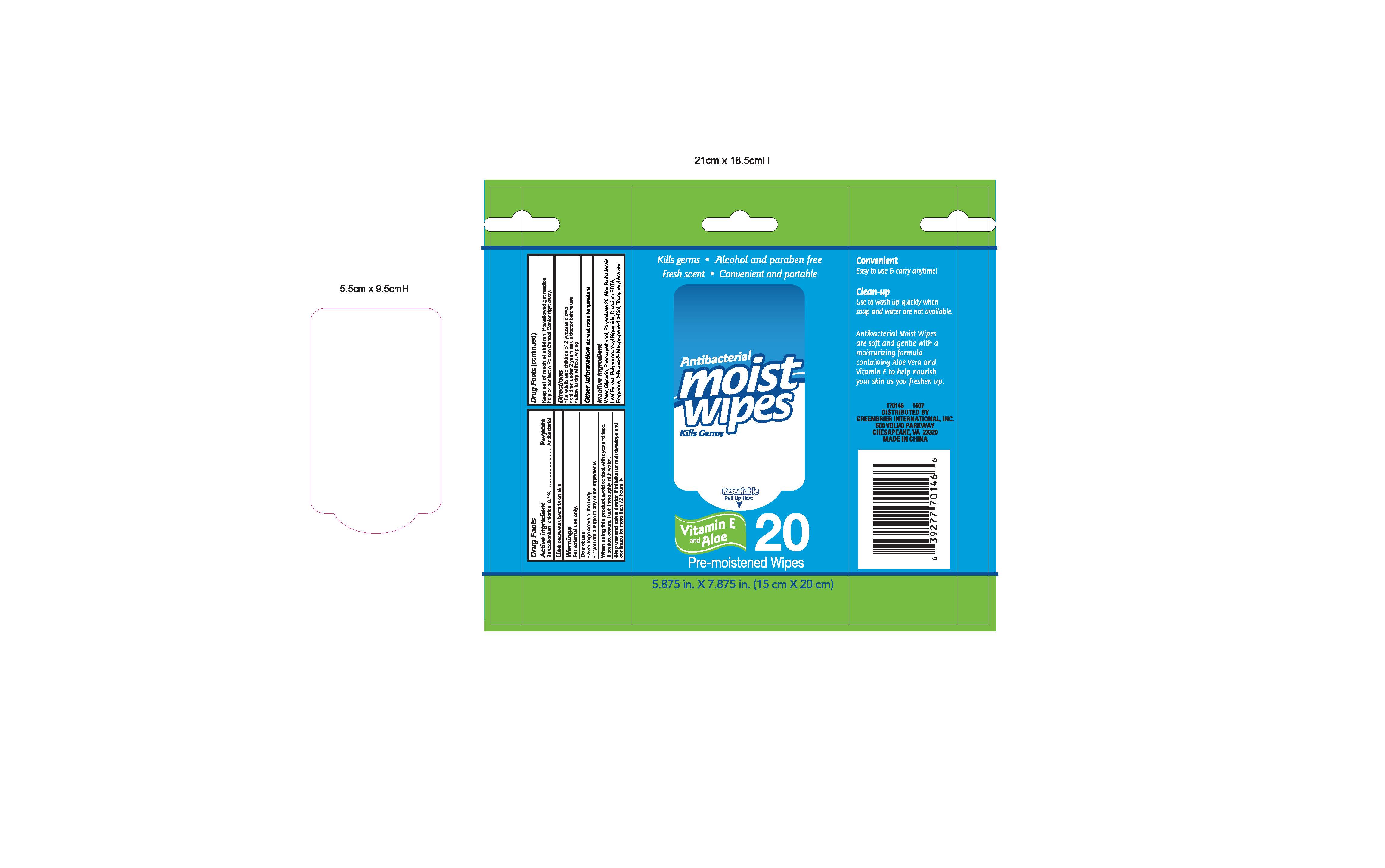 DRUG LABEL: moist wipes
NDC: 44019-005 | Form: LOTION
Manufacturer: Yinjing Medical Technology (Shanghai) Co., Ltd.
Category: otc | Type: HUMAN OTC DRUG LABEL
Date: 20160813

ACTIVE INGREDIENTS: BENZALKONIUM CHLORIDE .1 g/100 g
INACTIVE INGREDIENTS: WATER; POLYSORBATE 20; PHENOXYETHANOL; POLYAMINOPROPYL BIGUANIDE; ALOE VERA LEAF; BRONOPOL; DISODIUM EDTA-COPPER; GLYCERIN; .ALPHA.-TOCOPHEROL ACETATE

Active ingredient

Benzalkonium chloride 0.1%

Purpose

Antibacterial

INDICATIONS AND USAGE

Use decreases bacteria on skin

Warnings

For external use only

Do not use

-over large areas of the body

-if you are allergic to any of the ingredients

When using this product avoid contact with eyes and face.

If contact occurs, flush thoroughly with water.

Stop use and ask a doctor if irritation or rash develops and

continues for more than 72 hours

Keep out of reach of children. If swallowed, get medical

help or contact a Poison Control Center right away

Directions

-for adults and children of 2 years and over

-children under 2 years ask a doctor before using

-allow to dry without wiping

Other information store at room temperature

Inactive ingredient

Water, Glycerin, Phenoxyethanol, Polysorbate 20, Aloe Barabdensis

Leaf Extract, Polyaminopropyl Biguianide, Disodium EDTA,

Fragrance, 2-Bromo-2 Nitroporpane 1,3 Diol, Tocopheryl Acetate